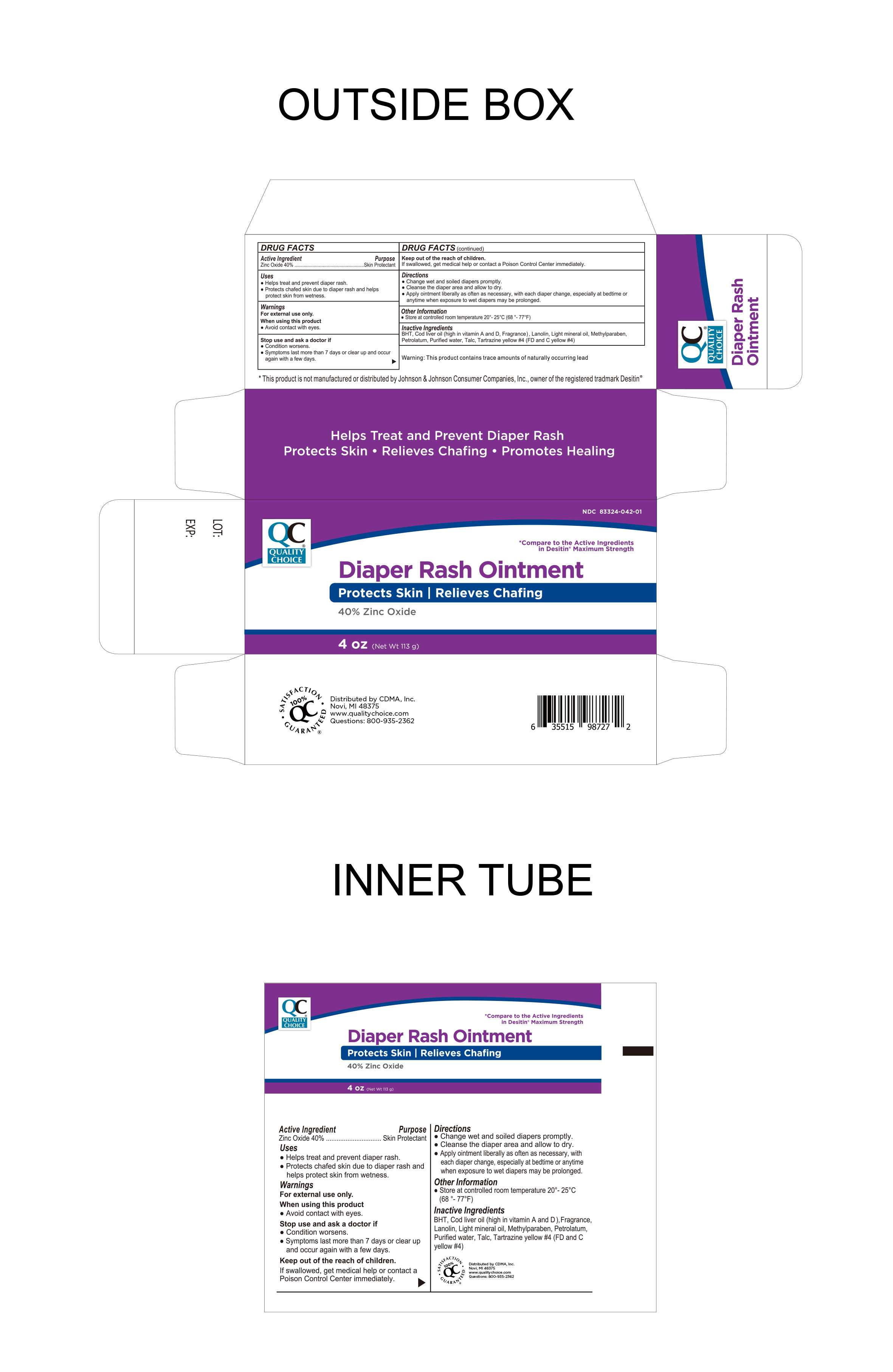 DRUG LABEL: Quality Choice Diaper Rash
NDC: 83324-042 | Form: OINTMENT
Manufacturer: Chain Drug Marketing Association Inc.
Category: otc | Type: HUMAN OTC DRUG LABEL
Date: 20241105

ACTIVE INGREDIENTS: ZINC OXIDE 40 g/100 g
INACTIVE INGREDIENTS: TALC; BUTYLATED HYDROXYTOLUENE; LANOLIN; FD&C YELLOW NO. 5; COD LIVER OIL; LIGHT MINERAL OIL; METHYLPARABEN; PETROLATUM; WATER

Quality Choice Diaper Rash Ointment

Active Ingredient

Zinc Oxide 40%

Purpose

Skin Protectant

Uses

- Helps treat and prevent diaper rash
- Protects chafed skin due to diaper rash and helps protect skin from wetness

Keep out of the reach of children.

If swallowed, get medical help or contact a Poison Control Center immediately.

Warnings

For External Use Only

When using this product

- Avoid contact with eyes

This product contains trace amounts of naturally occuring lead.

Directions

- Change wet and soiled diapers promptly
- Cleanse the diaper area and allow to dry
- Apply ointment liberally as often as necessary, with each diaper change, especially at bedtime or anytime when exposure to wet diapers may be prolonged.

Stop use and ask a doctor if

- Condition worsens
- Symptoms last more than 7 days or clear up and occur again with a few days

Other Information:

- Store at controlled room temperature 20° - 25°C (68° - 77°F)

Questions

1-800-935-2362

Inactive Ingredients

BHA, Cod liver oil (high in vitamin A and D), Fragrance, Lanolin, Mineral Oil, Methylparaben, Petrolatum, Purified water, Talc, Tartrazine yellow #4 (FD and C yellow #4)

Helps treat and prevent diaper rash. Protects skin. Relieves Chafing. Promotes Healing

Distributed by:

CDMA Inc.

Novi, MI. 48375 USA

www.qualitychoice.com

Questions: 800-935-2362

Other Information

This product is not manufactured or distributed by Johnson & Johnson Consumer Company Inc. owner of the registered trademark Desitin®.